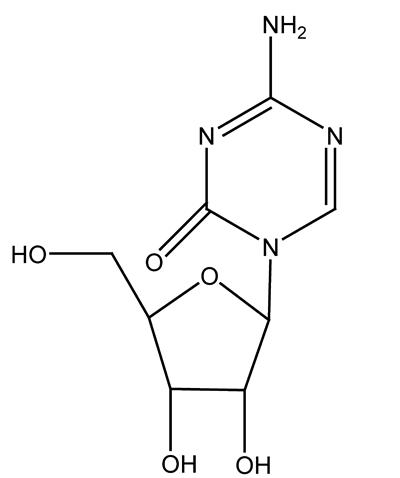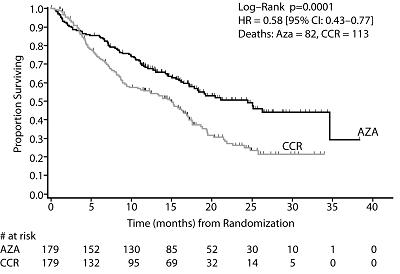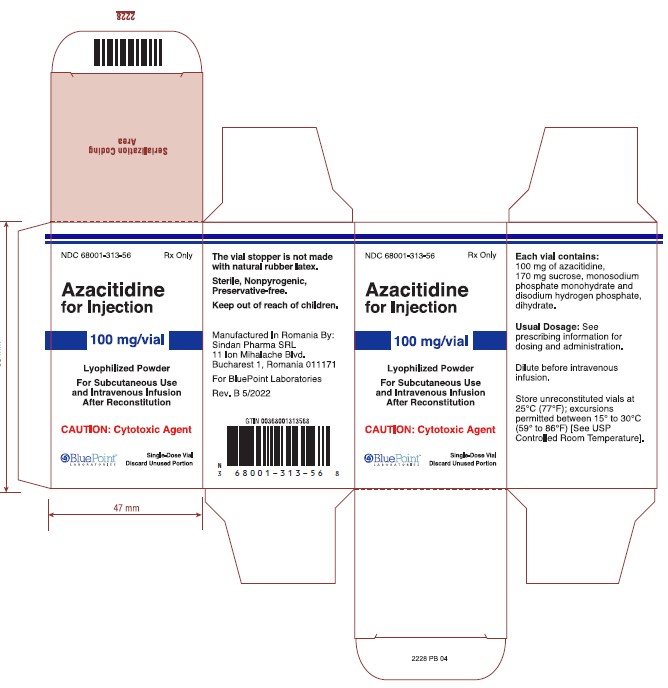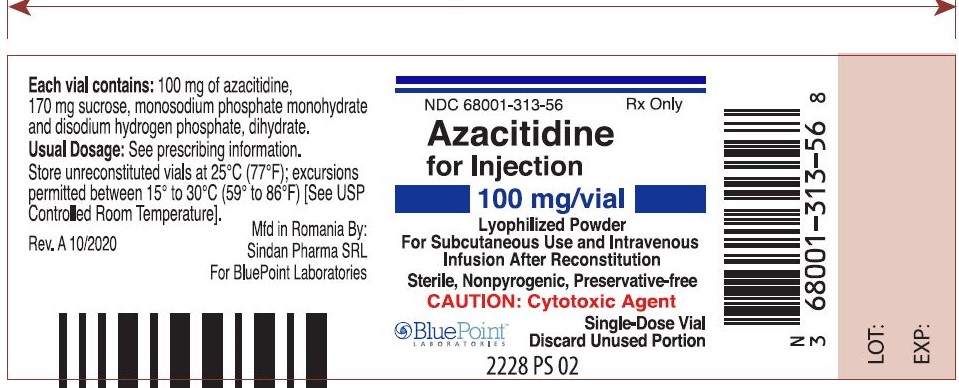 DRUG LABEL: Azacitidine
NDC: 68001-313 | Form: INJECTION, POWDER, LYOPHILIZED, FOR SOLUTION
Manufacturer: BluePoint Laboratories
Category: prescription | Type: HUMAN PRESCRIPTION DRUG LABEL
Date: 20250526

ACTIVE INGREDIENTS: AZACITIDINE 100 mg/1 1
INACTIVE INGREDIENTS: SUCROSE; SODIUM PHOSPHATE, MONOBASIC, MONOHYDRATE; SODIUM PHOSPHATE, DIBASIC, DIHYDRATE

HIGHLIGHTS OF PRESCRIBING INFORMATION

These highlights do not include all the information needed to use AZACITIDINE FOR INJECTION safely and effectively. See full prescribing information for AZACITIDINE FOR INJECTION.
AZACITIDINE for injection, for subcutaneous or intravenous use
Initial U.S. Approval: 2004

1 INDICATIONS AND USAGE

Azacitidine for Injection is a nucleoside metabolic inhibitor indicated for the treatment of adult patients with the following FAB myelodysplastic syndrome (MDS) subtypes: Refractory anemia (RA) or refractory anemia with ringed sideroblasts (RARS) (if accompanied by neutropenia or thrombocytopenia or requiring transfusions), refractory anemia with excess blasts (RAEB), refractory anemia with excess blasts in transformation (RAEB-T), and chronic myelomonocytic leukemia (CMMoL) (1).

2 DOSAGE AND ADMINISTRATION

- Do not substitute Azacitidine for Injection for oral azacitidine. The indications and dosing regimen for Azacitidine for Injection differ from that of oral azacitidine (2.1, 5.1).
- The recommended starting dosage for the first treatment cycle, for all patients regardless of baseline hematology values, is Azacitidine for Injection 75 mg/m2 daily for 7 days to be administered by subcutaneous injection or intravenous infusion. See full prescribing information for schedule for subsequent cycles. Premedicate for nausea and vomiting (2.2).
- Continue treatment as long as the patient continues to benefit (2.3).
- Monitor all patients for hematologic response and for renal toxicity; delay or reduce dosage as appropriate (2.4, 2.5, 2.6).

3 DOSAGE FORMS AND STRENGTHS

- For Injection: 100 mg as a lyophilized powder in single-dose vial for reconstitution (3).

4 CONTRAINDICATIONS

- Advanced malignant hepatic tumors (4).
- Hypersensitivity to azacitidine (4).

5 WARNINGS AND PRECAUTIONS

- Risks of Substitution with Other Azacitidine Products: Do not substitute Azacitidine for Injection for oral azacitidine (2.1, 5.1).
- Anemia, Neutropenia and Thrombocytopenia: Monitor complete blood counts (CBC) frequently (5.2).
- Hepatotoxicity: Patients with severe preexisting hepatic impairment are at higher risk for toxicity (5.3).
- Renal Toxicity: Monitor patients with renal impairment for toxicity since azacitidine and its metabolites are primarily excreted by the kidneys (5.4).
- Tumor Lysis Syndrome: Azacitidine for Injection may cause fatal or serious tumor lysis syndrome, including in patients with MDS. Assess baseline risk and monitor and treat as appropriate (5.5).
- Embryo-Fetal Toxicity: Can cause fetal harm. Advise patients of reproductive potential of the potential risk to a fetus and to use effective contraception (5.6, 8.1, 8.3).

6 ADVERSE REACTIONS

Most common adverse reactions (> 30%) in adult patients with MDS by subcutaneous route are: nausea, anemia, thrombocytopenia, vomiting, pyrexia, leukopenia, diarrhea, injection site erythema, constipation, neutropenia and ecchymosis. Most common adverse reactions by intravenous route also included petechiae, rigors, weakness and hypokalemia (6.1).

To report SUSPECTED ADVERSE REACTIONS, contact Actavis at 1-888-838-2872 or FDA at 1-800-FDA-1088 or www.fda.gov/medwatch.

8 USE IN SPECIFIC POPULATIONS

Lactation: Advise not to breastfeed (8.2).

Pediatric use information is approved for Celgene Corporation’s Vidaza®(azacitidine for injection). However due to Celgene Corporation’s marketing exclusivity rights, this drug product is not labeled with that information .

FULL PRESCRIBING INFORMATION

1 INDICATIONS AND USAGE

1.1 Myelodysplastic Syndromes (MDS)

Azacitidine for Injection is indicated for treatment of adult patients with the following French-American-British (FAB) myelodysplastic syndrome subtypes: refractory anemia (RA) or refractory anemia with ringed sideroblasts (if accompanied by neutropenia or thrombocytopenia or requiring transfusions), refractory anemia with excess blasts (RAEB), refractory anemia with excess blasts in transformation (RAEB-T), and chronic myelomonocytic leukemia (CMMoL).

Pediatric use information is approved for Celgene Corporation’s Vidaza®(azacitidine for injection). However due to Celgene Corporation’s marketing exclusivity rights, this drug product is not labeled with that information.

2 DOSAGE AND ADMINISTRATION

2.1 Important Administration Information

Do not substitute Azacitidine for Injection for oral azacitidine. The indications and dosing regimen for Azacitidine for Injection differ from that of oral azacitidine [ see Warnings and Precautions (5.1)] .

2.2 First Treatment Cycle for Adults

The recommended starting dose for the first treatment cycle, for all patients regardless of baseline hematology laboratory values, is 75 mg/m^2subcutaneously or intravenously, daily for 7 days.

Premedicate patients for nausea and vomiting.

Obtain complete blood counts, liver chemistries and serum creatinine prior to the first dose.

2.3 Subsequent Treatment Cycles for Adults

Repeat cycles every 4 weeks. The dose may be increased to 100 mg/m^2if no beneficial effect is seen after 2 treatment cycles and if no toxicity other than nausea and vomiting has occurred. It is recommended that patients be treated for a minimum of 4 to 6 cycles. However, complete or partial response may require additional treatment cycles. Treatment may be continued as long as the patient continues to benefit.

Monitor patients for hematologic response and renal toxicities [ see Warnings and Precautions (5.4)] and delay or reduce dosage if necessary as described below.

Pediatric use information is approved for Celgene Corporation’s Vidaza®(azacitidine for injection). However due to Celgene Corporation’s marketing exclusivity rights, this drug product is not labeled with that information.

2.4 Dosage Adjustment Based on Hematology Laboratory Values

- For adult patients with baseline (start of treatment) WBC greater than or equal to 3 x10^9/L, ANC greater than or equal to 1.5 x10^9/L, and platelets greater than or equal to 75 x10^9/L, adjust the dose as follows, based on nadir counts for any given cycle:

Nadir Counts |  | % Dose in the Next; Course
ANC (x10^9/L); Less than 0.5; 0.5 to 1.5; Greater than 1.5 | Platelets (x10^9/L); Less than 25; 25 to 50; Greater than 50 | 50%; 67%; 100%

- For adult patients whose baseline counts are WBC less than 3 x10^9/L, ANC less than 1.5 x10^9/L, or platelets less than 75 x10^9/L, base dose adjustments on nadir counts and bone marrow biopsy cellularity at the time of the nadir as noted below, unless there is clear improvement in differentiation (percentage of mature granulocytes is higher and ANC is higher than at onset of that course) at the time of the next cycle, in which case continue the current dose.

WBC or Platelet; Nadir; % decrease in; counts from baseline | Bone Marrow; Biopsy Cellularity at Time of Nadir; (%)
WBC or Platelet; Nadir; % decrease in; counts from baseline | 30 to 60 | 15 to 30 | Less than 15
50 to 75; Greater than 75 | % Dose in the Next Course
50 to 75; Greater than 75 | 100 | 50 | 33
50 to 75; Greater than 75 | 75 | 50 | 33

If a nadir as defined in the table above has occurred, give the next course 28 days after the start of the preceding course, provided that both the WBC and the platelet counts are greater than 25% above the nadir and rising. If a greater than 25% increase above the nadir is not seen by day 28, reassess counts every 7 days. If a 25% increase is not seen by day 42, reduce the scheduled dose by 50%.

Pediatric use information is approved for Celgene Corporation’s Vidaza®(azacitidine for injection). However due to Celgene Corporation’s marketing exclusivity rights, this drug product is not labeled with that information.

2.5 Dosage Adjustment Based on Serum Electrolytes and Renal Toxicity

If unexplained reductions in serum bicarbonate levels to less than 20 mEq/L occur, reduce the dosage by 50% for the next course.

If unexplained elevations of BUN or serum creatinine occur, delay the next cycle until values return to normal or baseline and reduce the dose by 50% for the next course [ see Warnings and Precautions (5.4)] .

2.6 Use in Geriatric Patients

Azacitidine and its metabolites are known to be substantially excreted by the kidney, and the risk of toxic reactions to this drug may be greater in patients with impaired renal function. Because elderly patients are more likely to have decreased renal function, select the dose carefully and monitor renal function [ see Warnings and Precautions (5.4)and Use in Specific Populations (8.5)] .

2.7 Preparation of Azacitidine for Injection

Azacitidine for Injection is a hazardous drug. Follow applicable special handling and disposal procedures.^1The Azacitidine for Injection vial is single-dose and does not contain any preservatives. Discard unused portions of each vial properly [ see How Supplied/Storage and Handling (16)] . Do not save any unused portions for later administration.

2.8 Instructions for Subcutaneous Administration

Reconstitute Azacitidine for Injection aseptically with 4 mL Sterile Water for Injection to obtain a concentration of 25 mg/mL. Inject the diluent slowly into the vial. Vigorously shake or roll the vial until a uniform suspension is achieved. The suspension will be cloudy. Do not filter the suspension after reconstitution. Doing so could remove the active substance.

Preparation for Immediate Subcutaneous Administration

For doses requiring more than 1 vial, divide the dose equally between the syringes (e.g., dose 150 mg = 6 mL, 2 syringes with 3 mL in each syringe) and inject into two separate sites. Due to retention in the vial and needle, it may not be feasible to withdraw all of the suspension from the vial. The product may be held at room temperature for up to 1 hour, but must be administered within 1 hour after reconstitution.

Preparation for Delayed Subcutaneous Administration

The reconstituted product may be kept in the vial or drawn into a syringe. For doses requiring more than 1 vial, divide the dose equally between the syringes (e.g., dose 150 mg = 6 mL, 2 syringes with 3 mL in each syringe) and inject into two separate sites. Due to retention in the vial and needle, it may not be feasible to withdraw all of the suspension from the vial. The product must be refrigerated immediately.

When Azacitidine for Injection is reconstituted using Sterile Water for Injection that has not been refrigerated, the reconstituted product may be held under refrigerated conditions (2°C to 8°C, 36°F to 46°F) for up to 12 hours.

When Azacitidine for Injection is reconstituted using refrigerated (2°C to 8°C, 36°F to 46°F) Sterile Water for Injection, the reconstituted product may be stored under refrigerated conditions (2°C to 8°C, 36°F to 46°F) for up to 30 hours.

After removal from refrigerated conditions, the suspension may be allowed to equilibrate to room temperature for up to 30 minutes prior to administration.

Subcutaneous Administration

To provide a homogeneous suspension, the contents of the dosing syringe must be re-suspended immediately prior to administration. To re-suspend, vigorously roll the syringe between the palms until a uniform, cloudy suspension is achieved.

Azacitidine for Injection suspension is administered subcutaneously. Doses greater than 4 mL should be divided equally into 2 syringes and injected into 2 separate sites. Rotate sites for each injection (thigh, abdomen, or upper arm). New injections should be given at least one inch from an old site and never into areas where the site is tender, bruised, red, or hard.

Suspension Stability

Azacitidine for Injection reconstituted with non-refrigerated Sterile Water for Injection for subcutaneous administration may be stored for up to 2 hours at 25°C (77°F) or for up to 12 hours between 2°C and 8°C (36°F and 46°F).

When reconstituted with refrigerated (2°C to 8°C, 36°F to 46°F) Sterile Water for Injection, it may be stored for 30 hours between 2°C and 8°C (36°F and 46°F).

2.9 Instructions for Intravenous Administration

Reconstitute the appropriate number of Azacitidine for Injection vials to achieve the desired dose. Reconstitute each vial with 10 mL Sterile Water for Injection. Vigorously shake or roll the vial until all solids are dissolved. The resulting solution will contain azacitidine 10 mg/mL. The solution should be clear. Parenteral drug product should be inspected visually for particulate matter and discoloration prior to administration, whenever solution and container permit.

Withdraw the required amount of Azacitidine for Injection solution to deliver the desired dose and inject into a 50 to 100 mL infusion bag of either 0.9% Sodium Chloride Injection or Lactated Ringer’s Injection.

Intravenous Solution Incompatibility

Azacitidine for Injection is incompatible with 5% Dextrose solutions, Hespan, or solutions that contain bicarbonate. These solutions have the potential to increase the rate of degradation of Azacitidine for Injection and should therefore be avoided.

Intravenous Administration

Azacitidine for Injection solution is administered intravenously. Administer the total dose over a period of 10 to 40 minutes. The administration must be completed within 1 hour of reconstitution of the Azacitidine for Injection vial.

Solution Stability

Azacitidine for Injection reconstituted for intravenous administration may be stored at 25°C (77°F), but administration must be completed within 1 hour of reconstitution.

Pediatric use information is approved for Celgene Corporation’s Vidaza®(azacitidine for injection). However due to Celgene Corporation’s marketing exclusivity rights, this drug product is not labeled with that information.

3 DOSAGE FORMS AND STRENGTHS

For injection: 100 mg as a lyophilized powder in single-dose vial for reconstitution.

4 CONTRAINDICATIONS

Azacitidine for Injection is contraindicated in patients with

- advanced malignant hepatic tumors [ see Warnings and Precautions (5.3)].
- a known hypersensitivity to azacitidine.

5 WARNINGS AND PRECAUTIONS

5.1 Risks of Substitution with Other Azacitidine Products

Due to substantial differences in the pharmacokinetic parameters [ see Clinical Pharmacology(12.3)], the recommended dose and schedule for Azacitidine for Injection are different from those of oral azacitidine products. Treatment of patients using Azacitidine for Injection at the recommended dosage of oral azacitidine may result in a fatal adverse reaction. Treatment of patients using oral azacitidine at the doses recommended for Azacitidine for Injection may not be effective. Do not substitute Azacitidine for Injection for oral azacitidine [ see Dosage and Administration (2.1)].

5.2 Anemia, Neutropenia and Thrombocytopenia

Azacitidine for Injection causes anemia, neutropenia and thrombocytopenia. Monitor complete blood counts frequently for response and/or toxicity, at a minimum, prior to each dosing cycle. After administration of the recommended dosage for the first cycle, adjust dosage for subsequent cycles based on nadir counts and hematologic response [ see Dosage and Administration (2.4)] .

Pediatric use information is approved for Celgene Corporation’s Vidaza®(azacitidine for injection). However due to Celgene Corporation’s marketing exclusivity rights, this drug product is not labeled with that information.

5.3 Hepatic Toxicity in Patients with Severe Pre-existing Hepatic Impairment

Because Azacitidine for Injection is potentially hepatotoxic in patients with severe pre-existing hepatic impairment, caution is needed in patients with liver disease. Patients with extensive tumor burden due to metastatic disease have been reported to experience progressive hepatic coma and death during azacitidine treatment, especially in such patients with baseline albumin less than 30 g/L.

Azacitidine for Injection is contraindicated in patients with advanced malignant hepatic tumors [ see Contraindications (4)] . Monitor liver chemistries prior to initiation of therapy and with each cycle.

Safety and effectiveness of Azacitidine for Injection in patients with MDS and hepatic impairment have not been studied as these patients were excluded from the clinical trials.

Pediatric use information is approved for Celgene Corporation’s Vidaza®(azacitidine for injection). However due to Celgene Corporation’s marketing exclusivity rights, this drug product is not labeled with that information.

5.4 Renal Toxicity

Renal toxicity ranging from elevated serum creatinine to renal failure and death have been reported in patients treated with intravenous azacitidine in combination with other chemotherapeutic agents for non-MDS conditions. In addition, renal tubular acidosis, defined as a fall in serum bicarbonate to less than 20 mEq/L in association with an alkaline urine and hypokalemia (serum potassium less than 3 mEq/L) developed in 5 patients with CML (an unapproved use) treated with azacitidine and etoposide.

Monitor serum creatinine and electrolytes prior to initiation of therapy and with each cycle. If unexplained reductions in serum bicarbonate less than 20 mEq/L or elevations of BUN or serum creatinine occur, reduce or hold the dose [see Dosage and Administration (2.5)].

Patients with renal impairment may be at increased risk for renal toxicity. Also, azacitidine and its metabolites are primarily excreted by the kidney. Therefore, monitor these patients closely for toxicity [see Dosage and Administration(2.5, 2.6)]. Patients with MDS and renal impairment were excluded from the clinical studies.

Pediatric use information is approved for Celgene Corporation’s Vidaza®(azacitidine for injection). However due to Celgene Corporation’s marketing exclusivity rights, this drug product is not labeled with that information.

5.5 Tumor Lysis Syndrome

Azacitidine for Injection may cause fatal or serious tumor lysis syndrome, including in patients with MDS. Tumor lysis syndrome may occur despite concomitant use of allopurinol. Assess baseline risk and monitor and treat as appropriate.

5.6 Embryo-Fetal Toxicity

Based on the mechanism of action and findings in animals, Azacitidine for Injection can cause fetal harm when administered to a pregnant woman. In animal studies, azacitidine caused adverse developmental outcomes when administered to mice and rats at doses of 3 to 12 mg/m^2and 6 mg/m^2(approximately 4% to 16% and 8%) of the recommended human daily dose of 75 mg/m^2, respectively.

Advise pregnant women of the potential risk to a fetus .Advise females of reproductive potential to use effective contraception during treatment with Azacitidine for Injection and for 6 months following the last dose. Advise males with female partners of reproductive potential to use effective contraception during treatment with Azacitidine for Injection and for 3 months following the last dose [see Use in Specific Populations (8.1, 8.3)] .

6 ADVERSE REACTIONS

The following clinically significant adverse reactions are described elsewhere in labeling:

- Anemia, Neutropenia and Thrombocytopenia [ see Warnings and Precautions (5.2)]
- Hepatotoxicity in Patients with Severe Pre-existing Hepatic Impairment [ see Warnings and Precautions (5.3)]
- Renal Toxicity [ see Warnings and Precautions (5.4)]
- Tumor Lysis Syndrome [ see Warnings and Precautions (5.5)]

6.1 Clinical Trials Experience

Because clinical trials are conducted under widely varying conditions, adverse reaction rates observed in the clinical trials of a drug cannot be directly compared to rates in the clinical trials of another drug and may not reflect the rates observed in practice.

The data described below reflect exposure to azacitidine in 443 MDS patients from 4 clinical studies. Study 1 was a supportive-care controlled trial (subcutaneous administration), Studies 2 and 3 were single arm studies (one with subcutaneous administration and one with intravenous administration), and Study 4 was an international randomized trial (subcutaneous administration) [ see Clinical Studies (14)] .

In Studies 1, 2 and 3, a total of 268 patients were exposed to azacitidine, including 116 exposed for 6 cycles (approximately 6 months) or more and 60 exposed for greater than 12 cycles (approximately one year). Azacitidine was studied primarily in supportive-care controlled and uncontrolled trials (n=150 and n=118, respectively). The population in the subcutaneous studies (n=220) was 23 to 92 years old (mean 66.4 years), 68% male, and 94% white, and had MDS or AML. The population in the intravenous study (n=48) was 35 to 81 years old (mean 63.1 years), 65% male, and 100% white. Most patients received average daily doses between 50 and 100 mg/m^2.

In Study 4, a total of 175 patients with higher-risk MDS (primarily RAEB and RAEB-T subtypes) were exposed to azacitidine. Of these patients, 119 were exposed for 6 or more cycles, and 63 for at least 12 cycles. The mean age of this population was 68.1 years (ranging from 42 to 83 years), 74% were male, and 99% were white. Most patients received daily azacitidine doses of 75 mg/m^2.

Most Commonly Occurring Adverse Reactions (Subcutaneous or Intravenous Route) in Adult Patients with MDS: nausea, anemia, thrombocytopenia, vomiting, pyrexia, leukopenia, diarrhea, injection site erythema, constipation, neutropenia, ecchymosis. The most common adverse reactions by intravenous route also included petechiae, rigors, weakness and hypokalemia.

Adverse Reactions Most Frequently (Greater Than 2%) Resulting in Clinical Intervention (Subcutaneous or Intravenous Route) in Adult Patients with MDS:

Discontinuation: leukopenia, thrombocytopenia, neutropenia.

Dose Held: leukopenia, neutropenia, thrombocytopenia, pyrexia, pneumonia, febrile neutropenia.

Dose Reduced: leukopenia, neutropenia, thrombocytopenia.

Table 1 presents adverse reactions occurring in at least 5% of patients treated with azacitidine (subcutaneous) in Studies 1 and 2. It is important to note that duration of exposure was longer for the azacitidine-treated group than for the observation group; patients received azacitidine for a mean of 11.4 months while mean time in the observation arm was 6.1 months.

Table 1: Most Frequently Observed Adverse Reactions (Greater Than or Equal To 5% in All Subcutaneous Azacitidine-Treated Patients; Studies 1 and 2)
 | Number (%) of Patients
Body System Adverse Reactiona | All Azacitidineb | Observationc
 | (N=220) | (N=92)
Blood and lymphatic system disorders
Anemia | 153 (70) | 59 (64)
Anemia aggravated | 12 (6) | 5 (5)
Febrile neutropenia | 36 (16) | 4 (4)
Leukopenia | 106 (48) | 27 (29)
Neutropenia | 71 (32) | 10 (11)
Thrombocytopenia | 144 (66) | 42 (46)
Gastrointestinal disorders
Abdominal tenderness | 26 (12) | 1 (1)
Constipation | 74 (34) | 6 (7)
Diarrhea | 80 (36) | 13 (14)
Gingival bleeding | 21 (10) | 4 (4)
Loose stools | 12 (6) | 0
Mouth hemorrhage | 11 (5) | 1 (1)
Nausea | 155 (71) | 16 (17)
Stomatitis | 17 (8) | 0
Vomiting | 119 (54) | 5 (5)
General disorders and administration site conditions
Chest pain | 36 (16) | 5 (5)
Injection site bruising | 31 (14) | 0
Injection site erythema | 77 (35) | 0
Injection site granuloma | 11 (5) | 0
Injection site pain | 50 (23) | 0
Injection site pigmentation changes | 11 (5) | 0
Injection site pruritus | 15 (7) | 0
Injection site reaction | 30 (14) | 0
Injection site swelling | 11 (5) | 0
Lethargy | 17 (8) | 2 (2)
Malaise | 24 (11) | 1 (1)
Pyrexia | 114 (52) | 28 (30)
Infections and infestations
Nasopharyngitis | 32 (15) | 3 (3)
Pneumonia | 24 (11) | 5 (5)
Upper respiratory tract infection | 28 (13) | 4 (4)
Injury, poisoning, and procedural complications
Post procedural hemorrhage | 13 (6) | 1 (1)
Metabolism and nutrition disorders
Anorexia | 45 (21) | 6 (7)
Musculoskeletal and connective tissue disorders
Arthralgia | 49 (22) | 3 (3)
Chest wall pain | 11 (5) | 0
Myalgia | 35 (16) | 2 (2)
Nervous system disorders
Dizziness | 41 (19) | 5 (5)
Headache | 48 (22) | 10 (11)
Psychiatric disorders
Anxiety | 29 (13) | 3 (3)
Insomnia | 24 (11) | 4 (4)
Respiratory, thoracic and mediastinal disorders
Dyspnea | 64 (29) | 11 (12)
Skin and subcutaneous tissue disorders
Dry skin | 11 (5) | 1 (1)
Ecchymosis | 67 (31) | 14 (15)
Erythema | 37 (17) | 4 (4)
Rash | 31 (14) | 9 (10)
Skin nodule | 11 (5) | 1 (1)
Urticaria | 13 (6) | 1 (1)
Vascular disorders
Hematoma | 19 (9) | 0
Hypotension | 15 (7) | 2 (2)
Petechiae | 52 (24) | 8 (9)
aMultiple terms of the same preferred terms for a patient are only counted once within each treatment group.
bIncludes adverse reactions from all patients exposed to azacitidine, including patients after crossing over from observations.
cIncludes adverse reactions from observation period only; excludes any adverse events after crossover to azacitidine.

Table 2 presents adverse reactions occurring in at least 5% of patients treated with azacitidine in Study 4. Similar to Studies 1 and 2 described above, duration of exposure to treatment with azacitidine was longer (mean 12.2 months) compared with best supportive care (mean 7.5 months).

Table 2: Most Frequently Observed Adverse Reactions (Greater Than or Equal To 5% in the Azacitidine -Treated Patients and the Percentage with NCI CTC Grade 3/4 Reactions; Study 4)
 | Number (%) of Patients
 | Any Grade |  | Grade 3/4
Body System Adverse Reactionsa | Azacitidine (N=175) | Best Supportive Care Only (N= 102) | Azacitidine (N=175) | Best Supportive Care Only (N= 102)
Blood and lymphatic system disorders
Anemia | 90 (51) | 45 (44) | 24 (14) | 9 (9)
Febrile neutropenia | 24 (14) | 10 (10) | 22 (13) | 7 (7)
Leukopenia | 32 (18) | 2 (2) | 26 (15) | 1 (1)
Neutropenia | 115 (66) | 29 (28) | 107 (61) | 22 (22)
Thrombocytopenia | 122 (70) | 35 (34) | 102 (58) | 29 (28)
Gastrointestinal disorders
Abdominal pain | 22 (13) | 7 (7) | 7 (4) | 0
Constipation | 88 (50) | 8 (8) | 2 (1) | 0
Dyspepsia | 10 (6) | 2 (2) | 0 | 0
Nausea | 84 (48) | 12 (12) | 3 (2) | 0
Vomiting | 47 (27) | 7 (7) | 0 | 0
General disorders and administration site conditions
Fatigue | 42 (24) | 12 (12) | 6 (3) | 2 (2)
Injection site bruising | 9 (5) | 0 | 0 | 0
Injection site erythema | 75 (43) | 0 | 0 | 0
Injection site hematoma | 11 (6) | 0 | 0 | 0
Injection site induration | 9 (5) | 0 | 0 | 0
Injection site pain | 33 (19) | 0 | 0 | 0
Injection site rash | 10 (6) | 0 | 0 | 0
Injection site reaction | 51 (29) | 0 | 1 (1) | 0
Pyrexia | 53 (30) | 18 (18) | 8 (5) | 1 (1)
Infections and infestations
Rhinitis | 10 (6) | 1 (1) | 0 | 0
Upper respiratory tract infection | 16 (9) | 4 (4) | 3 (2) | 0
Urinary tract infection | 15 (9) | 3 (3) | 3 (2) | 0
Investigations
Weight decreased | 14 (8) | 0 | 1 (1) | 0
Metabolism and nutrition disorders
Hypokalemia | 11 (6) | 3 (3) | 3 (2) | 3 (3)
Nervous system disorders
Lethargy | 13 (7) | 2 (2) | 0 | 1 (1)
Psychiatric disorders
Anxiety | 9 (5) | 1 (1) | 0 | 0
Insomnia | 15 (9) | 3 (3) | 0 | 0
Renal and urinary disorders
Hematuria | 11 (6) | 2 (2) | 4 (2) | 1 (1)
Respiratory, thoracic and mediastinal disorders
Dyspnea | 26 (15) | 5 (5) | 6 (3) | 2 (2)
Dyspnea exertional | 9 (5) | 1 (1) | 0 | 0
Pharyngolaryngeal pain | 11 (6) | 3 (3) | 0 | 0
Skin and subcutaneous tissue disorders
Erythema | 13 (7) | 3 (3) | 0 | 0
Petechiae | 20 (11) | 4 (4) | 2 (1) | 0
Pruritus | 21 (12) | 2 (2) | 0 | 0
Rash | 18 (10) | 1 (1) | 0 | 0
Vascular disorders
Hypertension | 15 (9) | 4 (4) | 2 (1) | 2 (2)
aMultiple reports of the same preferred term from a patient were only counted once within each treatment.

In Studies 1, 2 and 4 with subcutaneous administration of azacitidine, adverse reactions of neutropenia, thrombocytopenia, anemia, nausea, vomiting, diarrhea, constipation, and injection site erythema/reaction tended to increase in incidence with higher doses of azacitidine. Adverse reactions that tended to be more pronounced during the first 1 to 2 cycles of subcutaneous treatment compared with later cycles included thrombocytopenia, neutropenia, anemia, nausea, vomiting, injection site erythema/pain/bruising/reaction, constipation, petechiae, dizziness, anxiety, hypokalemia, and insomnia. There did not appear to be any adverse reactions that increased in frequency over the course of treatment.

Overall, adverse reactions were qualitatively similar between the intravenous and subcutaneous studies. Adverse reactions that appeared to be specifically associated with the intravenous route of administration included infusion site reactions (e.g. erythema or pain) and catheter site reactions (e.g. infection, erythema, or hemorrhage).

In clinical studies of either subcutaneous or intravenous azacitidine, the following serious adverse reactions occurring at a rate of less than 5% (and not described in Tables 1 or 2) were reported:

Blood and lymphatic system disorders:agranulocytosis, bone marrow failure, pancytopenia, splenomegaly.

Cardiac disorders:atrial fibrillation, cardiac failure, cardiac failure congestive, cardio-respiratory arrest, congestive cardiomyopathy.

Eye disorders:eye hemorrhage

Gastrointestinal disorders:diverticulitis, gastrointestinal hemorrhage, melena, perirectal abscess.

General disorders and administration site conditions:catheter site hemorrhage, general physical health deterioration, systemic inflammatory response syndrome.

Hepatobiliary disorders:cholecystitis.

Immune system disorders:anaphylactic shock, hypersensitivity.

Infections and infestations:abscess limb, bacterial infection, cellulitis, blastomycosis, injection site infection, Klebsiella sepsis, neutropenic sepsis, pharyngitis streptococcal, pneumonia Klebsiella, sepsis, septic shock, Staphylococcal bacteremia, Staphylococcal infection, toxoplasmosis.

Metabolism and nutrition disorders:dehydration.

Musculoskeletal and connective tissue disorders:bone pain aggravated, muscle weakness, neck pain.

Neoplasms benign, malignant and unspecified:leukemia cutis.

Nervous system disorders:cerebral hemorrhage, convulsions, intracranial hemorrhage.

Renal and urinary disorders:loin pain, renal failure.

Respiratory, thoracic and mediastinal disorders:hemoptysis, lung infiltration, pneumonitis, respiratory distress.

Skin and subcutaneous tissue disorders:pyoderma gangrenosum, rash pruritic, skin induration.

Surgical and medical procedures:cholecystectomy.

Vascular disorders:orthostatic hypotension.

Pediatric use information is approved for Celgene Corporation’s Vidaza® (azacitidine for injection). However due to Celgene Corporation’s marketing exclusivity rights, this drug product is not labeled with that information.

6.2 Postmarketing Experience

The following adverse reactions have been identified during postapproval use of azacitidine. Because these reactions are reported voluntarily from a population of uncertain size, it is not always possible to reliably estimate their frequency or establish a causal relationship to drug exposure.

- Interstitial lung disease
- Tumor lysis syndrome
- Injection site necrosis
- Sweet’s syndrome (acute febrile neutrophilic dermatosis)
- Necrotizing fasciitis (including fatal cases)
- Differentiation syndrome
- Pericardial effusion
- Pericarditis
- Cutaneous vasculitis

8 USE IN SPECIFIC POPULATIONS

8.1 Pregnancy

Risk Summary

Based on its mechanism of action and findings in animals, Azacitidine for Injection can cause fetal harm when administered to a pregnant woman [see Clinical Pharmacology (12.1)]. There are no data on the use of azacitidine in pregnant women. Azacitidine was teratogenic and caused embryo-fetal lethality in animals at doses lower than the recommended human daily dose (see Data).Advise pregnant women of the potential risk to the fetus.

The estimated background risk of major birth defects and miscarriage in the indicated population is unknown. All pregnancies have a background risk of birth defect, loss, or other adverse outcomes. In the U.S. general population, the estimated background risk of major birth defects and miscarriage in clinically recognized pregnancies is 2% to 4% and 15% to 20%, respectively.

Data

Animal Data

Early embryotoxicity studies in mice revealed a 44% frequency of intrauterine embryonal death (increased resorption) after a single IP (intraperitoneal) injection of 6 mg/m^2(approximately 8% of the recommended human daily dose on a mg/m^2basis) azacitidine on gestation day 10. Developmental abnormalities in the brain have been detected in mice given azacitidine on or before gestation day 15 at doses of ~3 to 12 mg/m^2(approximately 4% to 16% the recommended human daily dose on a mg/m^2basis).

In rats, azacitidine was clearly embryotoxic when given IP on gestation days 4 to 8 (postimplantation) at a dose of 6 mg/m^2(approximately 8% of the recommended human daily dose on a mg/m^2basis), although treatment in the preimplantation period (on gestation days 1 to 3) had no adverse effect on the embryos. Azacitidine caused multiple fetal abnormalities in rats after a single IP dose of 3 to 12 mg/m^2(approximately 8% the recommended human daily dose on a mg/m^2basis) given on gestation day 9, 10, 11 or 12. In this study azacitidine caused fetal death when administered at 3 to 12 mg/m^2on gestation days 9 and 10; average live animals per litter was reduced to 9% of control at the highest dose on gestation day 9. Fetal anomalies included: CNS anomalies (exencephaly/encephalocele), limb anomalies (micromelia, club foot, syndactyly, oligodactyly), and others (micrognathia, gastroschisis, edema, and rib abnormalities).

8.2 Lactation

Risk Summary

There is no information on the presence of azacitidine or its metabolites in human milk, the effects on a breast-fed child, or the effects on milk production. Because many drugs are excreted in human milk and because of the potential for tumorigenicity shown for azacitidine in animal studies [ see Nonclinical Toxicology (13.1)] and the potential for serious adverse reactions in a breastfeed child, advise women not to breastfeed during treatment with Azacitidine for Injection and for 1 week after the last dose.

8.3 Females and Males of Reproductive Potential

Based on its mechanism of action and findings in animals, Azacitidine for Injection can cause fetal harm when administered to a pregnant woman [ see Use in Specific Populations (8.1)] .

Pregnancy Testing

Verify the pregnancy status of females of reproductive potential prior to initiating Azacitidine for Injection.

Contraception

Females

Advise females of reproductive potential to use effective contraception during treatment with Azacitidine for Injection and for 6 months after the last dose [ see Use in Specific Populations (8.1)and Clinical Pharmacology (12.3)] .

Males

Based on genotoxicity findings, advise males with female partners of reproductive potential to use effective contraception during treatment with Azacitidine for Injection and for 3 months after the last dose [ see Nonclinical Toxicology (13.1)] .

Infertility

Based on animal data, azacitidine could have an effect on male or female fertility [ see Nonclinical Toxicology (13.1)] .

8.4 Pediatric Use

Safety and effectiveness of Azacitidine for Injection in pediatric patients with MDS have not been established.

Pediatric use information is approved for Celgene Corporation’s Vidaza®(azacitidine for injection). However due to Celgene Corporation’s marketing exclusivity rights, this drug product is not labeled with that information.

8.5 Geriatric Use

Of the total number of patients in Studies 1, 2 and 3, 62% were 65 years and older and 21% were 75 years and older. No overall differences in effectiveness were observed between these patients and younger patients. In addition, there were no relevant differences in the frequency of adverse reactions observed in patients 65 years and older compared to younger patients.

Of the 179 patients randomized to azacitidine in Study 4, 68% were 65 years and older and 21% were 75 years and older. Survival data for patients 65 years and older were consistent with overall survival results. The majority of adverse reactions occurred at similar frequencies in patients less than 65 years of age and patients 65 years of age and older.

Elderly patients are more likely to have decreased renal function. Monitor renal function in these patients [ see Dosage and Administration (2.6)and Warnings and Precautions (5.4)] .

10 OVERDOSAGE

One case of overdose with azacitidine was reported during clinical trials. A patient experienced diarrhea, nausea, and vomiting after receiving a single intravenous dose of approximately 290 mg/m^2, almost 4 times the recommended starting dose. The events resolved without sequelae, and the correct dose was resumed the following day. In the event of overdosage, the patient should be monitored with appropriate blood counts and should receive supportive treatment, as necessary. There is no known specific antidote for Azacitidine for Injection overdosage.

11 DESCRIPTION

Azacitidine is a nucleoside metabolic inhibitor. The molecular formula is C8H12N4O5. The molecular weight is

244. Azacitidine is 4-amino-1-β-D-ribofuranosyl-s-triazin-2(1H)-one. The structural formula is as follows:

Azacitidine is a white to almost white powder. Azacitidine was found to be insoluble in acetone, ethanol, and methyl ethyl ketone; slightly soluble in ethanol/water (50/50), propylene glycol, and polyethylene glycol; sparingly soluble in water, water saturated octanol, 5% dextrose in water, N-methyl-2-pyrrolidone, normal saline and 5% Tween 80 in water; and soluble in dimethylsulfoxide (DMSO).

Azacitidine for Injection is supplied in a sterile form for reconstitution as a suspension for subcutaneous injection or reconstitution as a solution with further dilution for intravenous infusion. Each vial of Azacitidine for Injection contains 100 mg of azacitidine, 170 mg sucrose, monosodium phosphate monohydrate and disodium hydrogen phosphate, dihydrate as a sterile lyophilized powder.

12 CLINICAL PHARMACOLOGY

12.1 Mechanism of Action

Azacitidine is a pyrimidine nucleoside analog of cytidine. Azacitidine is believed to exert its antineoplastic effects by causing hypomethylation of DNA and direct cytotoxicity on abnormal hematopoietic cells in the bone marrow. The concentration of azacitidine required for maximum inhibition of DNA methylation in vitro does not cause major suppression of DNA synthesis. Hypomethylation may restore normal function to genes that are critical for differentiation and proliferation. The cytotoxic effects of azacitidine cause the death of rapidly dividing cells, including cancer cells that are no longer responsive to normal growth control mechanisms. Non-proliferating cells are relatively insensitive to azacitidine.

12.2 Pharmacodynamics

Pediatric use information is approved for Celgene Corporation’s Vidaza®(azacitidine for injection). However due to Celgene Corporation’s marketing exclusivity rights, this drug product is not labeled with that information.

12.3 Pharmacokinetics

The area under the curve (AUC) and peak concentration (Cmax) of subcutaneous administration of azacitidine in patients with cancer were approximately dose proportional within the dose range of 25 mg/m^2(0.33 times the lowest approved recommended dosage) to 100 mg/m ^2(the maximum approved recommended dosage). The mean and standard deviation (SD) of Cmaxwas 750 ± 403 ng/mL after a single subcutaneous administration of 75 mg/m^2azacitidine. Multiple dosing at the recommended dose-regimen does not result in drug accumulation.

Absorption

Azacitidine is rapidly absorbed after subcutaneous administration with a median time to Cmax(Tmax) of 0.5 hour. The bioavailability of subcutaneous azacitidine relative to intravenous azacitidine is approximately 89%, based on AUC.

Distribution

Mean volume of distribution following intravenous dosing is 76 ± 26 L.

Elimination

Mean apparent subcutaneous clearance is 167 ± 49 L/hour and mean half-life after subcutaneous administration is 41 ± 8 minutes.

Excretion

Published studies indicate that urinary excretion is the primary route of elimination of azacitidine and its metabolites. Following intravenous administration of radioactive azacitidine to 5 cancer patients, the cumulative urinary excretion was 85% of the radioactive dose. Fecal excretion accounted for less than 1% of administered radioactivity over 3 days. Mean excretion of radioactivity in urine following subcutaneous administration of^14C-azacitidine was 50%. The mean elimination half-lives of total radioactivity (azacitidine and its metabolites) were similar after intravenous and subcutaneous administrations, about 4 hours.

Specific Populations

The effects of hepatic impairment, gender, or race/ethnicity on the pharmacokinetics of intravenous and subcutaneous azacitidine have not been studied.

Pediatric Patients

Pediatric use information is approved for Celgene Corporation’s Vidaza®(azacitidine for injection). However due to Celgene Corporation’s marketing exclusivity rights, this drug product is not labeled with that information.

Patients with Renal Impairment

In adult patients with cancer, the pharmacokinetics of azacitidine in 6 patients with normal renal function (CLcr >80 mL/min) and 6 patients with severe renal impairment (CLcr <30 mL/min) were compared following daily subcutaneous dosing (Days 1 through 5) at 75 mg/m^2/day. Severe renal impairment increased azacitidine exposure by approximately 70% after single and 41% after multiple subcutaneous administrations.). This increase in exposure was not correlated with an increase in adverse events. The exposure was similar to exposure in patients with normal renal function receiving 100 mg/m^2.

Drug Interaction Studies

No formal clinical drug interaction studies with azacitidine have been conducted.

In vitro Studies

Cytochrome P450 (CYP) Enzymes:An in vitro study at azacitidine concentrations up to 100 μM (IV Cmax= 10.6 μM) in human liver microsomes indicated that azacitidine does not cause any inhibition of CYP isoforms CYP1A2, CYP2B6, CYP2C8, CYP2C9, CYP2C19, CYP2D6, CYP3A4, or CYP2E1 at clinically achievable concentrations.

In vitro studies with human cultured hepatocytes indicate that azacitidine at concentrations of 1.0 μM to 100 μM does not induce CYP 1A2, 2C19, or 3A4/5.

Transporter Systems:An in vitro study with LLC-PK1 cells expressing P-glycoprotein (P-gp) indicated that azacitidine is not a substrate or inhibitor of P-gp.

Azacitidine does not inhibit, breast cancer resistance protein (BCRP), organic anion transporters (OAT) OAT1 and OAT3, organic anion transporting polypeptides (OATP) OATP1B1 and OATP1B3, or organic cation transporter (OCT) OCT2 at clinically relevant concentrations.

13 NONCLINICAL TOXICOLOGY

13.1 Carcinogenesis, Mutagenesis, Impairment of Fertility

The potential carcinogenicity of azacitidine was evaluated in mice and rats. Azacitidine induced tumors of the hematopoietic system in female mice at 2.2 mg/kg (6.6 mg/m^2, approximately 8% the recommended human daily dose on a mg/m^2basis) administered IP three times per week for 52 weeks. An increased incidence of tumors in the lymphoreticular system, lung, mammary gland, and skin was seen in mice treated with azacitidine IP at 2.0 mg/kg (6.0 mg/m^2, approximately 8% the recommended human daily dose on a mg/m^2basis) once a week for 50 weeks. A tumorigenicity study in rats dosed twice weekly at 15 or 60 mg/m^2(approximately 20% to 80% the recommended human daily dose on a mg/m^2basis) revealed an increased incidence of testicular tumors compared with controls.

The mutagenic and clastogenic potential of azacitidine was tested in in vitro bacterial systems Salmonella typhimurium strains TA100 and several strains of trpE8, Escherichia coli strains WP14 Pro, WP3103P, WP3104P, and CC103; in in vitro forward gene mutation assay in mouse lymphoma cells and human lymphoblast cells; and in an in vitro micronucleus assay in mouse L5178Y lymphoma cells and Syrian hamster embryo cells. Azacitidine was mutagenic in bacterial and mammalian cell systems. The clastogenic effect of azacitidine was shown by the induction of micronuclei in L5178Y mouse cells and Syrian hamster embryo cells.

Administration of azacitidine to male mice at 9.9 mg/m^2(approximately 9% the recommended human daily dose on a mg/m^2basis) daily for 3 days prior to mating with untreated female mice resulted in decreased fertility and loss of offspring during subsequent embryonic and postnatal development. Treatment of male rats 3 times per week for 11 or 16 weeks at doses of 15 to 30 mg/m^2(approximately 20% to 40%, the recommended human daily dose on a mg/m^2basis) resulted in decreased weight of the testes and epididymides, and decreased sperm counts accompanied by decreased pregnancy rates and increased loss of embryos in mated females. In a related study, male rats treated for 16 weeks at 24 mg/m^2resulted in an increase in abnormal embryos in mated females when examined on day 2 of gestation.

14 CLINICAL STUDIES

Myelodysplastic Syndromes (MDS)

Study 1 was a randomized, open-label, controlled trial carried out in 53 U.S. sites that compared the safety and efficacy of subcutaneous azacitidine plus supportive care with supportive care alone (“observation”) in adult patients with any of the five FAB subtypes of myelodysplastic syndromes (MDS): refractory anemia (RA), RA with ringed sideroblasts (RARS), RA with excess blasts (RAEB), RAEB in transformation (RAEB-T), and chronic myelomonocytic leukemia (CMMoL). RA and RARS patients were included if they met one or more of the following criteria: required packed RBC transfusions; had platelet counts less than or equal to 50 x 10^9/L; required platelet transfusions; or were neutropenic (ANC less than 1 x 10^9/L) with infections requiring treatment with antibiotics. Patients with acute myelogenous leukemia (AML) were not intended to be included. Supportive care allowed in this study included blood transfusion products, antibiotics, antiemetics, analgesics and antipyretics. The use of hematopoietic growth factors was prohibited. Baseline patient and disease characteristics are summarized in Table 3; the 2 groups were similar.

Azacitidine was administered at a subcutaneous dose of 75 mg/m^2daily for 7 days every 4 weeks. The dose was increased to 100 mg/m^2if no beneficial effect was seen after 2 treatment cycles. The dose was decreased and/or delayed based on hematologic response or evidence of renal toxicity. Patients in the observation arm were allowed by protocol to cross over to azacitidine if they had increases in bone marrow blasts, decreases in hemoglobin, increases in red cell transfusion requirements, or decreases in platelets, or if they required a platelet transfusion or developed a clinical infection requiring treatment with antibiotics. For purposes of assessing efficacy, the primary endpoint was response rate (as defined in Table 4).

Of the 191 patients included in the study, independent review (adjudicated diagnosis) found that 19 had the diagnosis of AML at baseline. These patients were excluded from the primary analysis of response rate, although they were included in an intent-to-treat (ITT) analysis of all patients randomized. Approximately 55% of the patients randomized to observation crossed over to receive azacitidine treatment.

Table 3. Baseline Demographics and Disease Characteristics
 | Azacitidine; (N=99) | Observation; (N=92)
Gender (n%)
Male | 72 (72.7) | 60 (65.2)
Female | 27 (27.3) | 32 (34.8)
Race (n%)
White | 93 (93.9) | 85 (92.4)
Black | 1 (1.0) | 1 (1.1)
Hispanic | 3 (3.0) | 5 (5.4)
Asian/Oriental | 2 (2.0) | 1 (1.1)
Age (years)
N | 99 | 91
Mean ± SD | 67.3 ± 10.39 | 68.0 ± 10.23
Range | 31 to 92 | 35 to 88
Adjudicated MDS diagnosis at study entry (n%)
RA | 21 (21.2) | 18 (19.6)
RARS | 6 (6.1) | 5 (5.4)
RAEB | 38 (38.4) | 39 (42.4)
RAEB-T | 16 (16.2) | 14 (15.2)
CMMoL | 8 (8.1) | 7 (7.6)
AML | 10 (10.1) | 9 (9.8)
Transfusion product used in 3 months before study entry (n%)
Any transfusion product | 70 (70.7) | 59 (64.1)
Blood cells, packed human | 66 (66.7) | 55 (59.8)
Platelets, human blood | 15 (15.2) | 12 (13.0)
Hetastarch | 0(0.0) | 1(1.1)
Plasma protein fraction | 1(1.0) | 0(0.0)
Other | 2(2.0) | 2(2.2)

Table 4. Response Criteria
 |  | RA | RARS | RAEB | RAEB-T | CMMoL
Complete Response; (CR),duration; ≥4 weeks | Marrow | <5% blasts
Complete Response; (CR),duration; ≥4 weeks | Marrow
Complete Response; (CR),duration; ≥4 weeks | Peripheral; Blood | Normal CBC if abnormal at baseline; Absence of blasts in the peripheral circulation
Partial; Response; (PR),duration; ≥4 weeks | Marrow | No marrow; requirements |  | ≥50% decrease in blasts; Improvement of marrow dyspoiesis
Partial; Response; (PR),duration; ≥4 weeks | Peripheral; Blood | ≥50% restoration in the deficit from normal levels of baseline white cells,; hemoglobin and platelets if abnormal at baseline; No blasts in the peripheral circulation; For CMMoL, if WBC is elevated at baseline, a ≥75% reduction in the excess; count over the upper limit of normal

The overall response rate (CR + PR) of 15.7% in azacitidine -treated patients without AML (16.2% for all azacitidine randomized patients including AML) was statistically significantly higher than the response rate of 0% in the observation group (p<0.0001) (Table 5). The majority of patients who achieved either CR or PR had either 2 or 3 cell line abnormalities at baseline (79%; 11/14) and had elevated bone marrow blasts or were transfusion dependent at baseline. Patients responding to azacitidine had a decrease in bone marrow blasts percentage, or an increase in platelets, hemoglobin or WBC. Greater than 90% of the responders initially demonstrated these changes by the 5thtreatment cycle. All patients who had been transfusion dependent became transfusion independent during PR or CR. The mean and median duration of clinical response of PR or better was estimated as 512 and 330 days, respectively; 75% of the responding patients were still in PR or better at completion of treatment. Response occurred in all MDS subtypes as well as in patients with adjudicated baseline diagnosis of AML.

Table 5. Response Rates
 | Azacitidine; (N=89) | Observation Before; Crossover; (N=83)
Response | n (%) | n (%) | P value
Overall (CR+PR) | 14 (15.7) | 0 (0.0) | (<0.0001)
Complete (CR) | 5 (5.6) | 0 (0.0) | (0.06)
Partial (PR) | 9 (10.1) | 0 (0.0) | --

Patients in the observation group who crossed over to receive azacitidine treatment (47 patients) had a response rate of 12.8%.

Study 2, a multi-center, open-label, single-arm study of 72 patients with RAEB, RAEB-T, CMMoL, or AML was also carried out. Treatment with subcutaneous azacitidine resulted in a response rate (CR + PR) of 13.9%, using criteria similar to those described above. The mean and median duration of clinical response of PR or better was estimated as 810 and 430 days, respectively; 80% of the responding patients were still in PR or better at the time of completion of study involvement. In Study 3, another open-label, single-arm study of 48 patients with RAEB, RAEB-T, or AML, treatment with intravenous azacitidine resulted in a response rate of 18.8%, again using criteria similar to those described above. The mean and median duration of clinical response of PR or better was estimated as 389 and 281 days, respectively; 67% of the responding patients were still in PR or better at the time of completion of treatment. Response occurred in all MDS subtypes as well as in patients with adjudicated baseline diagnosis of AML in both of these studies. Azacitidine dosage regimens in these 2 studies were similar to the regimen used in the controlled study.

Benefit was seen in patients who did not meet the criteria for PR or better, but were considered “improved.” About 24% of azacitidine-treated patients were considered improved, and about 2/3 of those lost transfusion dependence. In the observation group, only 5/83 patients met criteria for improvement; none lost transfusion dependence. In all 3 studies, about 19% of patients met criteria for improvement with a median duration of 195 days.

Study 4 was an international, multicenter, open-label, randomized trial in MDS patients with RAEB, RAEB-T or modified CMMoL according to FAB classification and Intermediate-2 and High risk according to IPSS classification. Of the 358 patients enrolled in the study, 179 were randomized to receive azacitidine plus best supportive care (BSC) and 179 were randomized to receive conventional care regimens (CCR) plus BSC (105 to BSC alone, 49 to low dose cytarabine and 25 to chemotherapy with cytarabine and anthracycline). The primary efficacy endpoint was overall survival.

The azacitidine and CCR groups were comparable for baseline parameters. The median age of patients was 69 years (range was 38 to 88 years), 98% were Caucasian, and 70% were male. At baseline, 95% of the patients were higher risk by FAB classification: RAEB (58%), RAEB-T (34%), and CMMoL (3%). By IPSS classification, 87% were higher risk: Int-2 (41%), High (47%). At baseline, 32% of patients met WHO criteria for AML.

Azacitidine was administered subcutaneously at a dose of 75 mg/m^2daily for 7 consecutive days every 28 days (which constituted one cycle of therapy). Patients continued treatment until disease progression, relapse after response, or unacceptable toxicity. Azacitidine patients were treated for a median of 9 cycles (range 1 to 39), BSC only patients for a median of 7 cycles (range 1 to 26), low dose cytarabine patients for a median of 4.5 cycles (range 1 to 15), and chemotherapy with cytarabine and anthracycline patients for a median of 1 cycle (range 1 to 3, i.e. induction plus 1 or 2 consolidation cycles).

In the Intent-to-Treat analysis, patients treated with azacitidine demonstrated a statistically significant difference in overall survival as compared to patients treated with CCR (median survival of 24.5 months vs. 15.0 months; stratified log-rank p=0.0001). The hazard ratio describing this treatment effect was 0.58 (95% CI: 0.43, 0.77).

Kaplan-Meier Curve of Time to Death from Any Cause: (Intent-to-Treat Population)

Key: AZA = azacitidine; CCR = conventional care regimens; CI = confidence interval; HR = Hazard Ratio

Azacitidine treatment led to a reduced need for red blood cell transfusions (see Table 6). In patients treated with azacitidine who were RBC transfusion dependent at baseline and became transfusion independent, the median duration of RBC transfusion independence was 13.0 months.

Table 6. Effect of Azacitidine on RBC Transfusions in MDS Patients
Efficacy Parameter | Azacitidine plus BSC (n= 179) | Conventional Care Regimens (n= 179)
Number and percent of patients who were transfusion dependent at baseline who became transfusion independent on treatment^1; Number and percent of patients who were transfusion-independent at baseline who became transfusion-dependent on treatment | 50/111 (45.0%); (95% CI: 35.6%, 54.8%); 10/68 (14.7%); (95% CI: 7.3%, 25.4%) | 13/114 (11.4%); (95% CI: 6.2%, 18.7%); 28/65 (43.1%); (95% CI: 30.9%, 56.0%)
^1A patient was considered RBC transfusion independent during the treatment period if the patient had no RBC transfusions during any 56 consecutive days or more during the treatment period. Otherwise, the patient was considered transfusion dependent.
Pediatric use information is approved for Celgene Corporation’s Vidaza®(azacitidine for injection). However due to Celgene Corporation’s marketing exclusivity rights, this drug product is not labeled with that information.

15 REFERENCES

1. “OSHA Hazardous Drugs.” OSHA. http://www.osha.gov/SLTC/hazardousdrugs/index.html

16 HOW SUPPLIED/STORAGE AND HANDLING

How Supplied

Azacitidine for Injection is supplied as 100 mg of lyophilized powder in single-dose vials packaged in cartons of 1 vial (NDC 68001-313-56).

Storage

Store unreconstituted vials at 25°C (77°F); excursions permitted to 15° to 30°C (59° to 86°F) [See USP Controlled Room Temperature].

Discard unused portion.

Handling and Disposal

Azacitidine for Injection is a hazardous drug. Follow applicable special handling and disposal procedures.^1Sterile, Nonpyrogenic, Preservative-free.

This vial stopper is not made with natural rubber latex.

17 PATIENT COUNSELING INFORMATION

Hepatic Toxicity in Patients with Severe Pre-Existing Hepatic Impairment

Instruct patients to inform their healthcare provider about any underlying liver disease [ see Warnings and Precautions (5.3)].

Renal Toxicity

Instruct patients to inform their healthcare provider about any underlying renal disease [ see Warnings and Precautions (5.4)].

Embryo-Fetal Toxicity

Advise pregnant women and females of reproductive potential of the potential risk to a fetus. Advise females of reproductive potential to inform their healthcare provider of a known or suspected pregnancy [ see Warnings and Precautions (5.6) and Use in Specific Populations (8.1)] .

Advise females of reproductive potential to use effective contraception during treatment with Azacitidine for Injection and for 6 months after the last dose [ see Use in Specific Populations (8.3)].

Advise male patients with female partners of reproductive potential to use effective contraception during treatment with Azacitidine for Injection and for 3 months after the last dose [ see Use in Specific Populations (8.3)] .

Lactation

Advise women not to breastfeed during treatment with Azacitidine for Injection and for 1 week after the last dose [ see Use in Specific Populations (8.2)].

Infertility

Advise males and females of the potential for reduced fertility from Azacitidine for Injection [ see Use in Specific Populations (8.3)and Nonclinical Toxicology (13.1)].

Manufactured In Romania By:
Sindan Pharma SRL
11 Ion Mihalache Blvd.
Bucharest 1, Romania 011171

For BluePoint Laboratories

Rev. E 12/2024